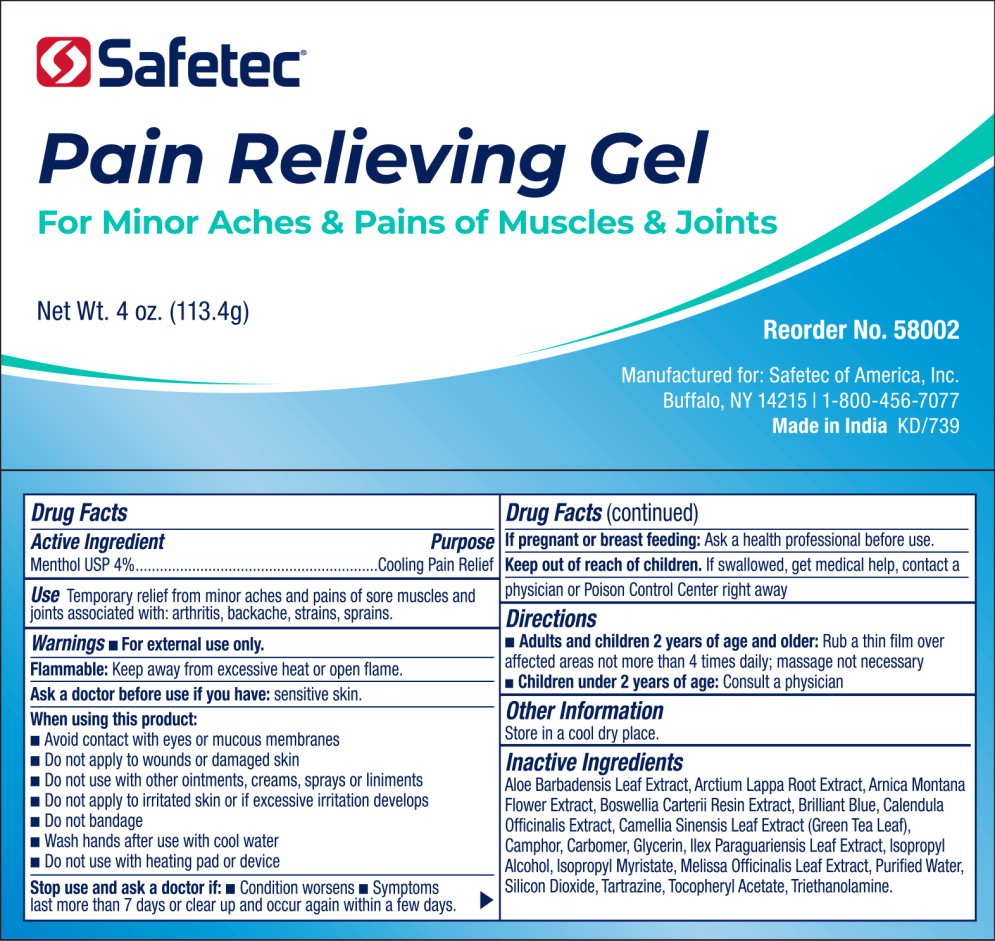 DRUG LABEL: Pain Relieving
NDC: 61010-4403 | Form: GEL
Manufacturer: Safetec of America, Inc.
Category: otc | Type: HUMAN OTC DRUG LABEL
Date: 20240205

ACTIVE INGREDIENTS: MENTHOL 4 g/100 g
INACTIVE INGREDIENTS: ALOE VERA LEAF; ARCTIUM LAPPA ROOT; ARNICA MONTANA; FRANKINCENSE; FD&C BLUE NO. 1; CALENDULA OFFICINALIS FLOWER; GREEN TEA LEAF; CAMPHOR (NATURAL); CARBOMER HOMOPOLYMER TYPE C (ALLYL PENTAERYTHRITOL CROSSLINKED); GLYCERIN; ILEX PARAGUARIENSIS LEAF; ISOPROPYL ALCOHOL; MELISSA OFFICINALIS LEAF; WATER; SILICON DIOXIDE; FD&C YELLOW NO. 5; .ALPHA.-TOCOPHEROL ACETATE; TRIETHYLAMINE

61010-4403-1

Drug Facts

Active Ingredient

Menthol USP 4%

Purpose

Cooling Pain Relief

Use

Temporary relief from minor aches and pains of sore muscles and joints associated with: arthritis, backache, strains sprains.

Warnings

- For external use only.

Flammable:Keep away from excessive heat or open flame.

Ask a doctor before use if you have:sensitive skin.

When using this product:

- Avoid contact with eyes or mucous membranes
- Do not apply to wounds or damaged skin
- Do not use with other ointments, creams, sprays or liniments
- Do not apply to irritated skin or if excessive irritation develops
- Do not bandage
- Wash hands after use with cool water
- Do not use with heating pad or device

Stop use and ask a doctor if:

- Condition worsens
- Symptoms last more than 7 days or clear up and occur again within a few days.

PREGNANCY OR BREAST FEEDING

If pregnant or breast feeding: Ask a health professional before use.

Keep out of reach of children. If swallowed, get medical help, contact a physician or Poison Control Center right away

Directions

- Adults and children 2 years of age and older: Rub a thin film over affected areas not more than 4 times daily; massage not necessary
- Children under 2 years of age:Consult a physician

Other Information

Store in a cool dry place.

Inactive Ingredients

Aloe Barbadensis Leaf Extract, Arctium Lappa Root Extract, Arnica Montana Flower Extract, Boswellia Carterii Resin Extract, Brilliant Blue, Calendula Officinalis Extract, Camellia Sinensis Leaf Extract (Green Tea Leal), Camphor, Carbomer, Glycerin, Ilex Paraguariensis Leaf Extract, Isopropyl Alcohol, Isopropyl Myristate, Melissa Officinalis Leaf Extract, Purified Water, Silicon Dioxide, Tartrazine, TocopheryI Acetate, Triethanolamine.

PACKAGE LABEL

Principal Display Panel – 4 oz Pain Relieving Gel

Safetec®

Pain Relieving Gel

For Minor Aches & Pains of Muscles & Joints

Net Wt. 4 oz. (113.4g)

Reorder No. 58002

Manufactured for: Safetec of America, Inc.

Buffalo, NY 14215 I 1-800-456-7077

Made in IndiaKD/739